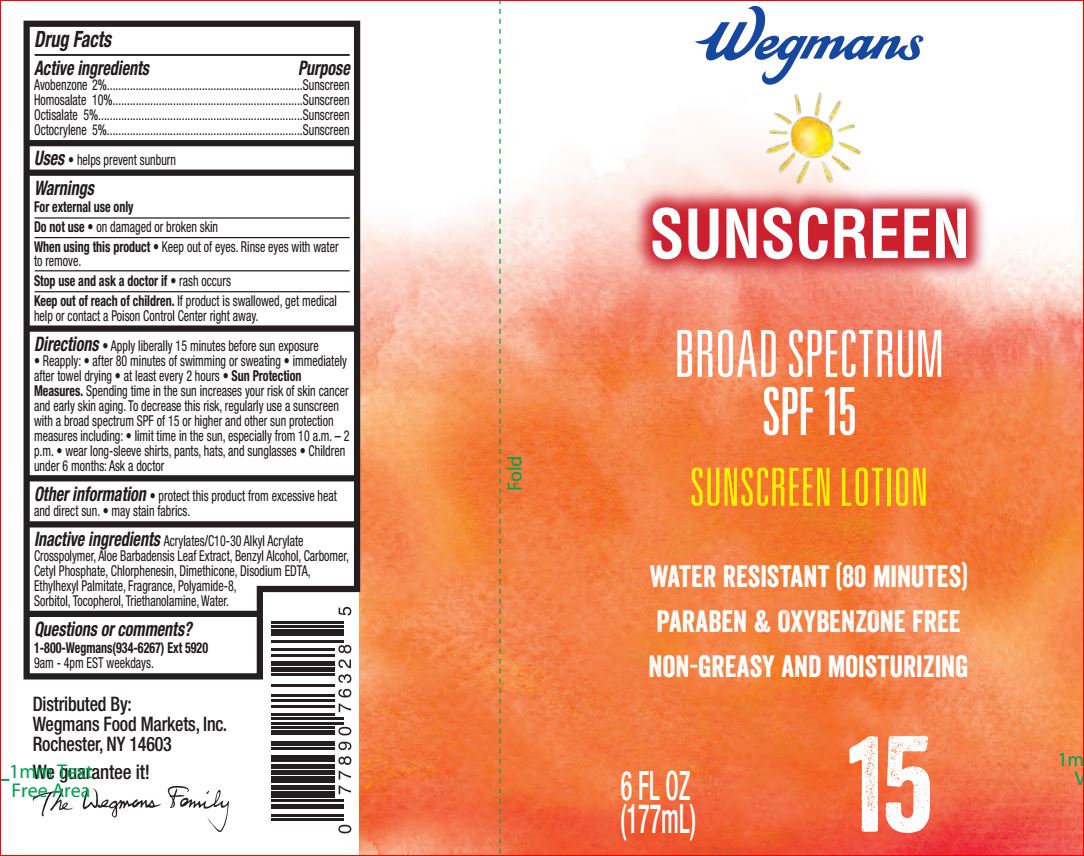 DRUG LABEL: Sunscreen SPF 15
NDC: 47124-119 | Form: LOTION
Manufacturer: Wegman
Category: otc | Type: HUMAN OTC DRUG LABEL
Date: 20180816

ACTIVE INGREDIENTS: AVOBENZONE 2 g/100 mL; HOMOSALATE 10 g/100 mL; OCTISALATE 5 g/100 mL; OCTOCRYLENE 5 g/100 mL
INACTIVE INGREDIENTS: CARBOMER COPOLYMER TYPE B (ALLYL PENTAERYTHRITOL CROSSLINKED); ALOE VERA LEAF; BENZYL ALCOHOL; CARBOMER HOMOPOLYMER TYPE C (ALLYL PENTAERYTHRITOL CROSSLINKED); CETYL PHOSPHATE; CHLORPHENESIN; DIMETHICONE; EDETATE DISODIUM; ETHYLHEXYL PALMITATE; LP-20; SORBITOL; .ALPHA.-TOCOPHEROL ACETATE, DL-; TROLAMINE; WATER

Drug Facts

Active Ingredients

2% Avobenzone

10% Homosalate

5% Octisalate

5% Octocrylene

Purpose

Sunscreen

Uses

- helps prevent sunburn

Warnings

For external use only

Do not use

on damaged or broken skin

When using this product

keep out of eyes. Rinse with water to remove.

Stop use and ask a doctor

if rash occurs

Keep out of reach of children.

If product is swallowed, get medical help or contact a Poison Control Center right away.

Directions

- apply liberally 15 minutes before sun exposure
- reapply: after 80 minutes of swimming or sweating, immediately after towel drying, at least every 2 hours
- Sun Protection Measures. Spending time in the sun increases your risk of skin cancer and early skin aging. To decrease this risk, regularly use a sunscreen with a broad spectrum SPF of 15 or higher and other sun protection measures including:
- limit time in the sun, especially from 10 a.m. - 2 p.m.
- wear long-sleeve shirts, pants, hats, and sunglasses
- children under 6 months: Ask a doctor

Inactive Ingredients

Acrylates/C10-30 Alkyl Acrylate Crosspolymer, Aloe Barbadensis Leaf Juice, Benzyl Alcohol, Carbomer, Cetyl Phosphate, Chlorphenesin, Dimethicone, Disodium EDTA, Ethylhexyl Palmitate, Fragrance, Polyamide-8, Sorbitol, Tocopherol, Triethanodamine, Water

Other Information

- protect this product from excessive heat and direct sun
- may stain fabrics